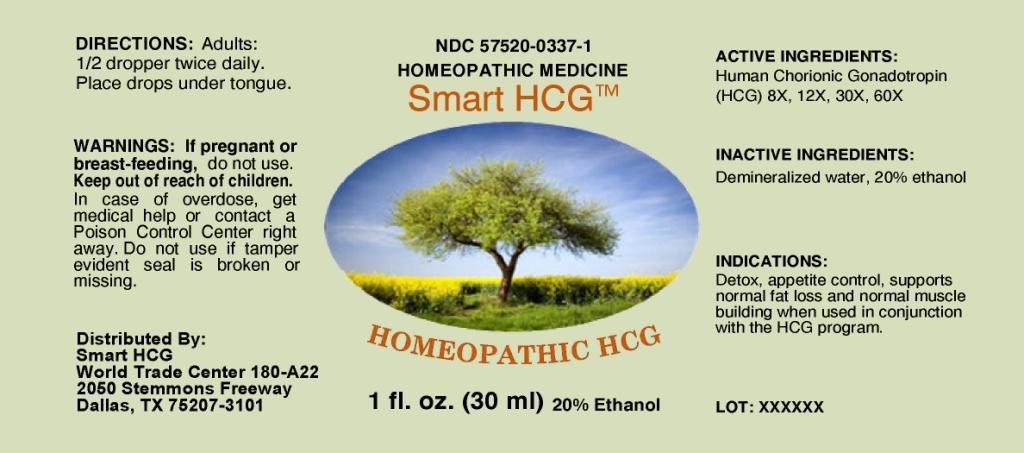 DRUG LABEL: Smart HCG
NDC: 57520-0337 | Form: LIQUID
Manufacturer: Apotheca Company
Category: homeopathic | Type: HUMAN OTC DRUG LABEL
Date: 20101110

ACTIVE INGREDIENTS: HUMAN CHORIONIC GONADOTROPIN 60 [hp_X]/1 mL
INACTIVE INGREDIENTS: WATER; ALCOHOL

Smart HCG

ACTIVE INGREDIENT

ACTIVE INGREDIENTS: Human chorionic gonadotropin (hcg) 8X, 12X, 30X, 60X.

PURPOSE

INDICATIONS: Detox, appetite control, supports normal fat loss and normal muscle building when used in conjunction with the HCG program.

WARNINGS

WARNINGS: If pregnant or breast-feeding, do not use.

Keep out of reach of children. In case of overdose, get medical help or contact a Poison Control Center right away.

Do not use if tamper evident seal is broken or missing.

DOSAGE AND ADMINISTRATION

DIRECTIONS: Adults: 1/2 dropper twice daily. Place drops under tongue.

INACTIVE INGREDIENTS: Demineralized water, 20% Ethanol.

KEEP OUT OF REACH OF CHILDREN. In case of overdose, get medical help or contact a Poison Control Center right away.

INDICATIONS AND USAGE

INDICATIONS: Detox, appetite control, supports normal fat loss and normal muscle building when used in conjunction with the HCG program.

QUESTIONS

Distributed By:

Smart HCG

World Trade Center 180-A22

2050 Stemmons Freeway

Dallas, TX 75207-3101

PACKAGE LABEL

NDC 57520-0337-1

HOMEOPATHIC MEDICINE

Smart HCG

HOMEOPATHIC HCG

1 fl. oz. (30 ml)